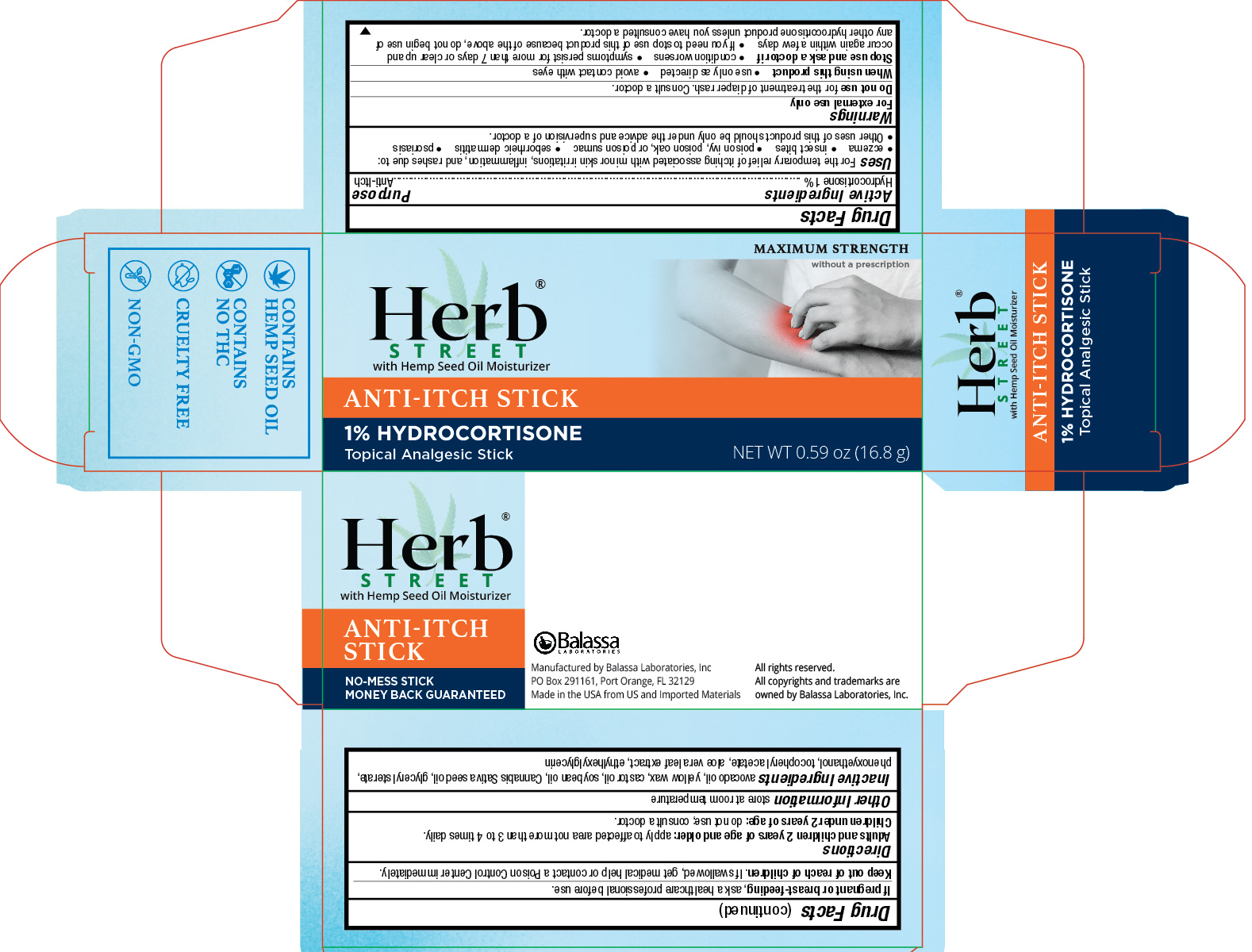 DRUG LABEL: Herb Street Anti-Itch Stick
NDC: 10107-429 | Form: STICK
Manufacturer: Balassa Laboratories Inc.
Category: otc | Type: HUMAN OTC DRUG LABEL
Date: 20241001

ACTIVE INGREDIENTS: HYDROCORTISONE 0.01 g/1 g
INACTIVE INGREDIENTS: YELLOW WAX; AVOCADO OIL; SOYBEAN OIL; CASTOR OIL; CANNABIS SATIVA SEED OIL; GLYCERYL MONOSTEARATE; PHENOXYETHANOL; .ALPHA.-TOCOPHEROL ACETATE; ALOE VERA LEAF; ETHYLHEXYLGLYCERIN

Herb Street Anti-Itch Stick

Active Ingredient

Hydrocortisone 1%

Purpose

Anti-Itch

Uses

For the temporary relief of itching associated with minor skin irritations, inflammation, and rashes due to:

- eczema
- insect bites
- poison ivy, poison oak, or poison sumac
- seborrheic dermatitis
- psoriasis
- Other uses of this product should only be under the advice and supervision of a doctor.

Warnings

For external use only

Do not use

for the treatment of diaper rash. Consult a doctor.

When using this product

- use only as directed
- avoid contact with eyes

Stop use and ask a doctor if

- condition worsens
- symptoms persist for more than 7 days or clear up and occur again within a few days
- If you need to stop use of the product because of the above, do not begin use of any other hydrocortisone product unless you have consulted a doctor.

If pregnant or breast-feeding

ask a healthcare professional before use.

Keep out of reach of children.

If swallowed, get medical help or contact a Poison Control Center immediately.

Directions

Adults and children 2 years of age and older:apply to affected area not more than 3 to 4 times daily.
Children under 2 years of age: do not use; consult a doctor.

Other Information

store at room temperature

Inactive Ingredients

avocado oil, yellow wax, castor oil, soybean oil, Cannabis Sativa seed oil, glyceryl stearate, phenoxyethanol, tocopheryl acetate, aloe vera leaf extract, ethylhexylglycerin

PRINCIPAL DISPLAY PANEL - 16.8 g Tube in Carton

Herb Street with Hemp Seed Oil Moisturizer

Anti-Itch Stick

1% Hydrocortisone

Topical Analgesic Stick

NET WT 0.59 oz (16.8 g)

No Mess Stick

Money Back Guranteed

Manufactured by Balassa Laboratories, Inc.

PO Box 291161, Port Orange, FL 32129

Made in the USA from US and Imported Materials

All rights reserved.

All copyrights and trademarks are owned by Balassa Laboratories, Inc.